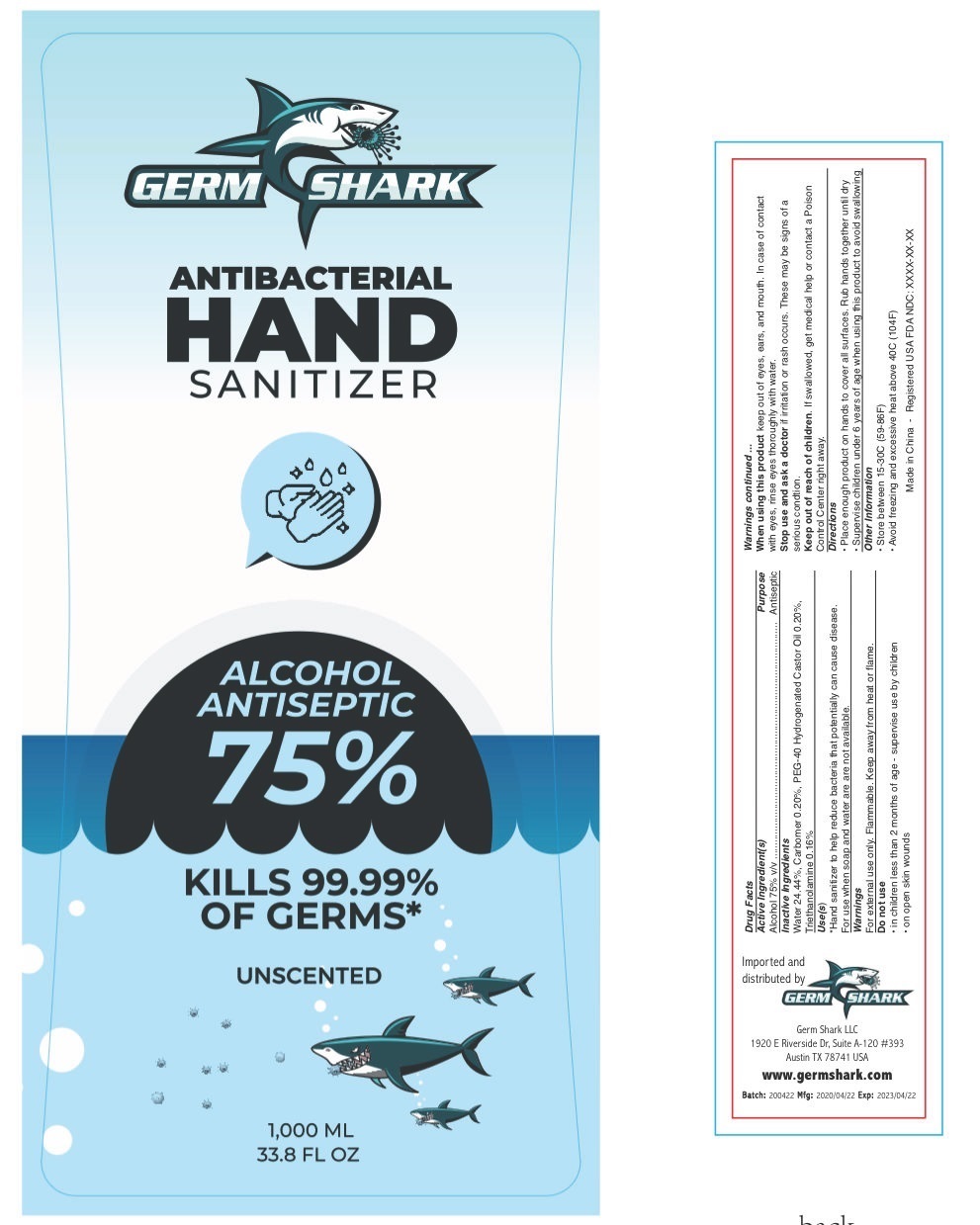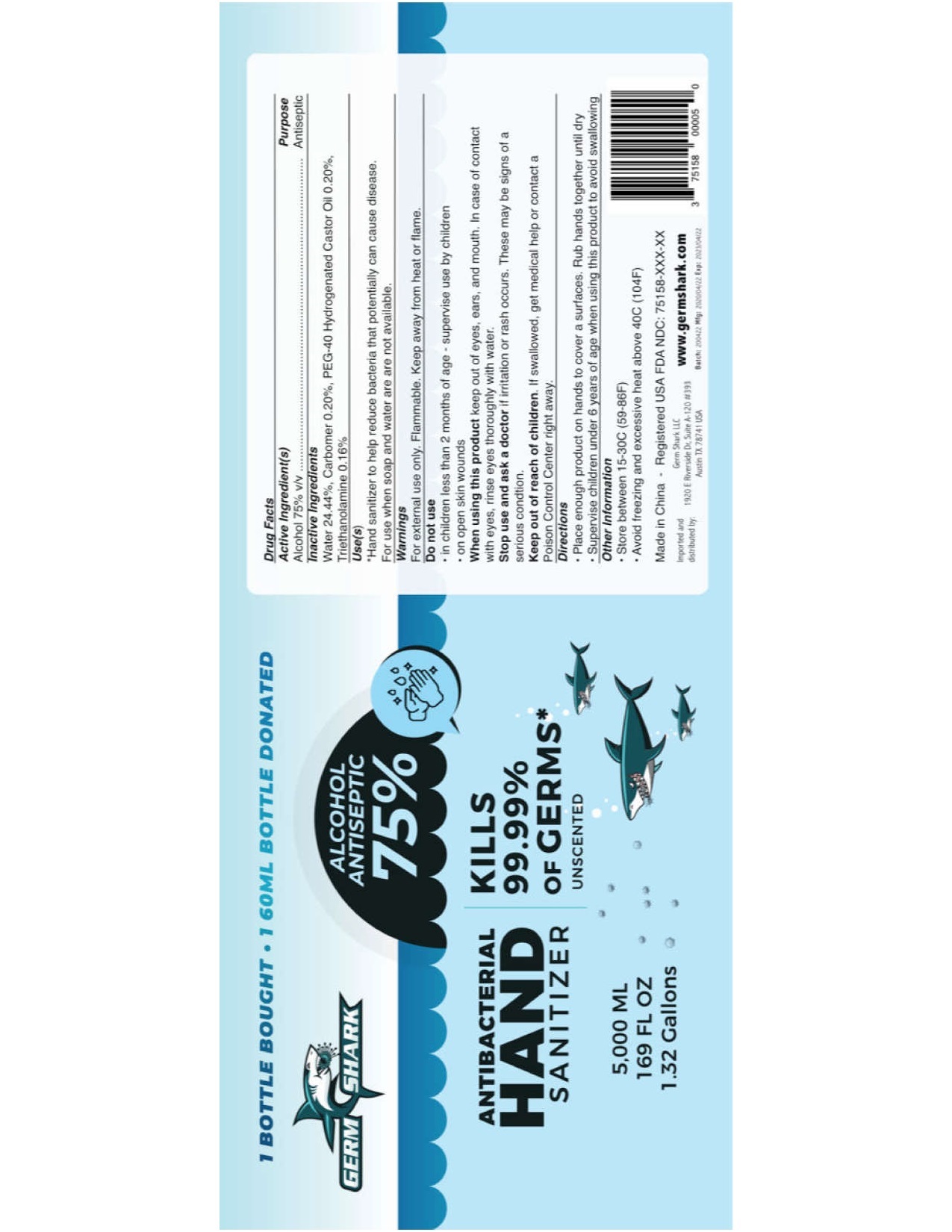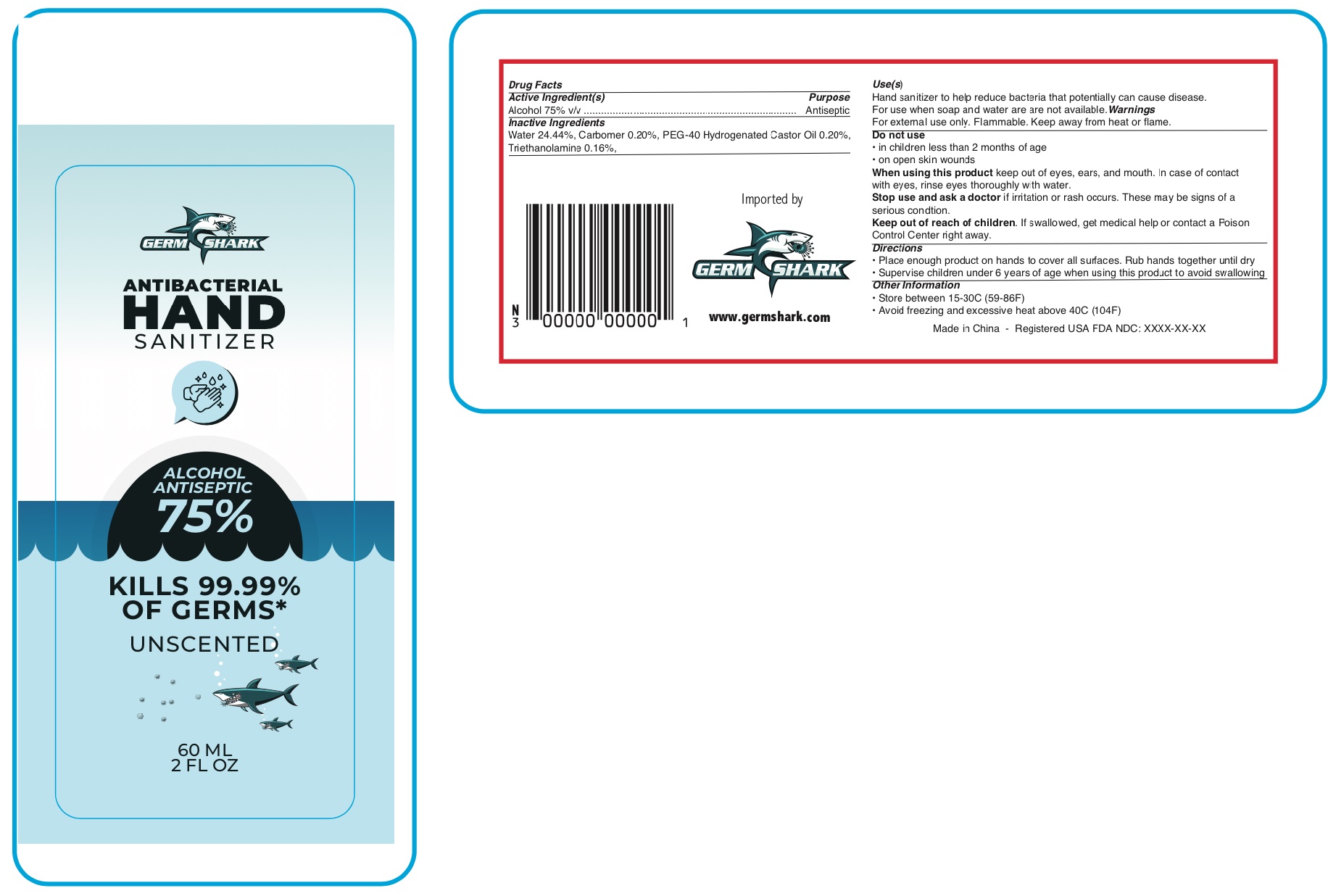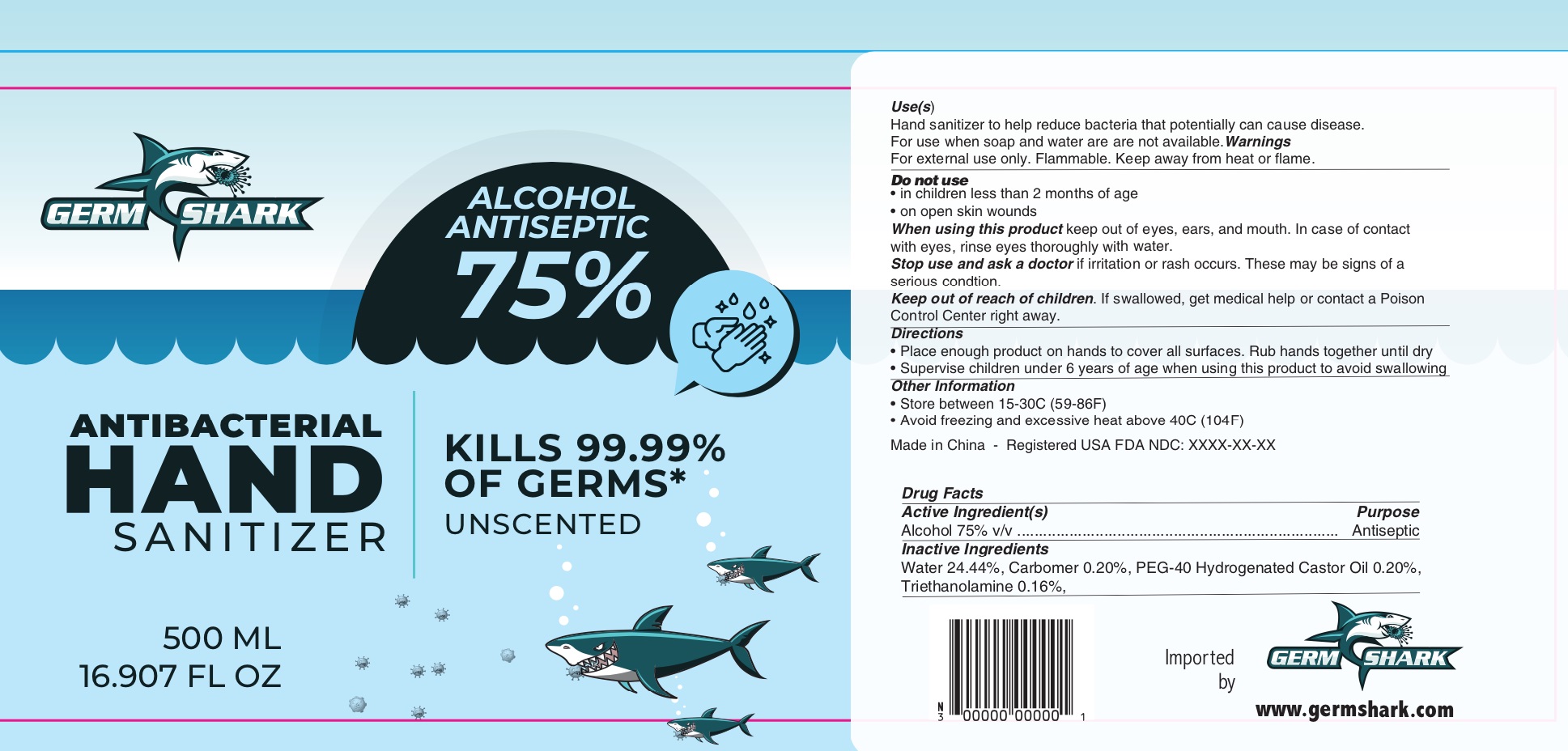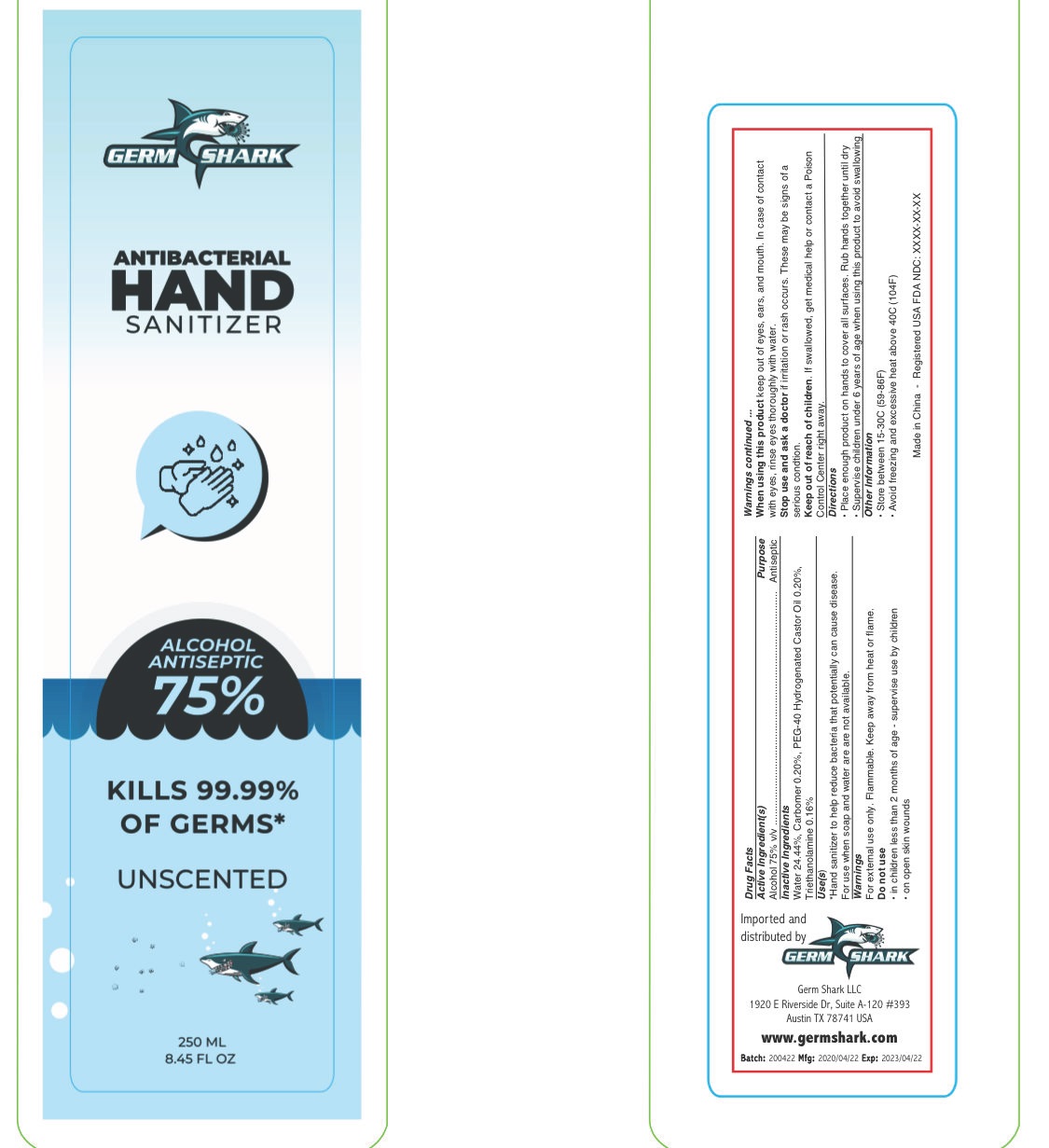 DRUG LABEL: Germ Shark Antibacterial Hand Sanitizer
NDC: 75158-001 | Form: LIQUID
Manufacturer: Germ Shark, LLC
Category: otc | Type: HUMAN OTC DRUG LABEL
Date: 20201105

ACTIVE INGREDIENTS: ALCOHOL 0.75 mL/1 mL
INACTIVE INGREDIENTS: WATER; CARBOMER HOMOPOLYMER, UNSPECIFIED TYPE; POLYOXYL 40 HYDROGENATED CASTOR OIL; TROLAMINE

Germ Shark Antibacterial Hand Sanitizer

Active Ingredient(s)

Alcohol 75% v/v

Purpose

Antiseptic

Inactive Ingredients

Water 24.44%, Carbomer 0.20%, PEG-40 Hydrogenated Castor Oil 0.20%, Triethanolamine 0.16%.

Use(s)

Hand sanitizer to help reduce bacteria that potentially can cause disease.

For use when soap and water are are not available.

Warnings

For external use only. Flammable. Keep away from heat or flame.

Do not use

- in children less than 2 months of age
- on open skin wounds

When using this product

keep out of eyes, ears, and mouth. In case of contact with eyes. rinse thoroughly with water.

Stop use and ask a doctor

if irritation or rash occurs. These may be signs of a serious condition.

Keep out of reach of children.

If swallowed, get medical help or contact a Poison Control Center right away.

Directions

- Place enough product on hands to cover all surfaces. Rub hands together until dry
- Supervise children under 6 years of age when using this product to avoid swallowing

Other Information

- Store between 15-30C (59-86F)
- Avoid freezing and excessive heat above 40C (104F)